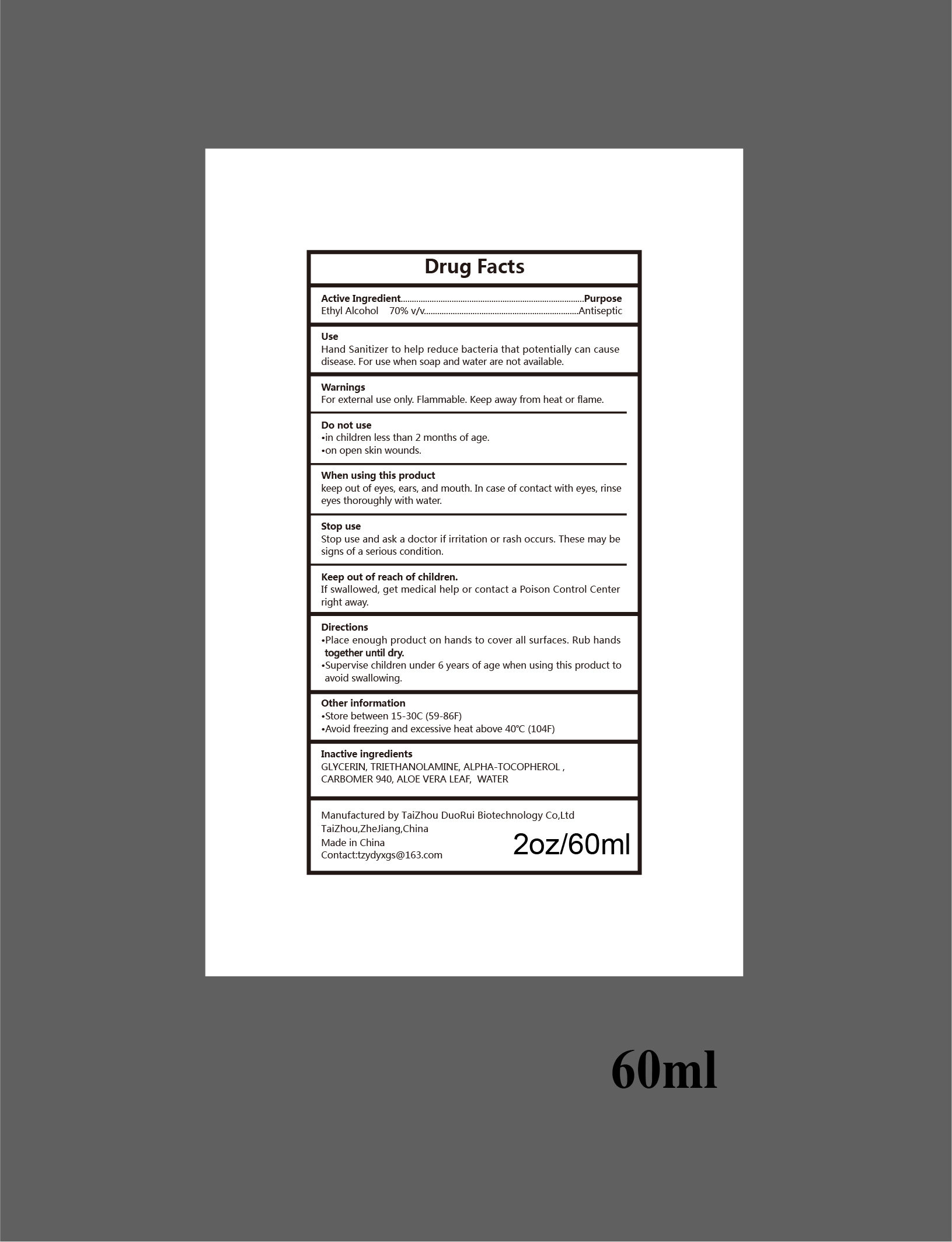 DRUG LABEL: Hand Sanitizer
NDC: 80800-003 | Form: SOLUTION
Manufacturer: Taizhou Duorui Biotechnology Co., Ltd.
Category: otc | Type: HUMAN OTC DRUG LABEL
Date: 20201111

ACTIVE INGREDIENTS: ALCOHOL 70 mL/100 mL
INACTIVE INGREDIENTS: GLYCERIN; CARBOMER 940; ALOE VERA LEAF; .ALPHA.-TOCOPHEROL; TROLAMINE; WATER

80800-003

Active Ingredient(s)

Ethyl Alcohol 70% v/v

Purpose

Antiseptic

Use

Hand sanitizer to help decrease bacteria that potentially can cause disease

For use when soap and water are not available

Warnings

For external use only. Flammable. Keep away from heat or flame

Do not use

- In children less than 2 months of age
- On open skin wounds

When using this product, keep out of eyes, ears or mouth. In case of contact with eyes, rinse eyes thoroughly with water.

Stop use and ask a doctor if irritation or rash occurs, these may be signs of a serious condition.

Keep out of reach of children. If swallowed, get medical help or contact a Poison Control Center right away.

Directions

- Place enough product on hands to cover all surfaces
- Rub hands together until dry
- Supervise children under 6 years of age when using this product to avoid swallowing

Other Information

Store between 15-30C (59-86F)

Avoid freezing or excessive heat above 40C (104F)

Inactive ingredients

Glycerin, Triethanolamine, Carbomer 940, Aloe Vera Leaf, Alpha Tocopherol, Water